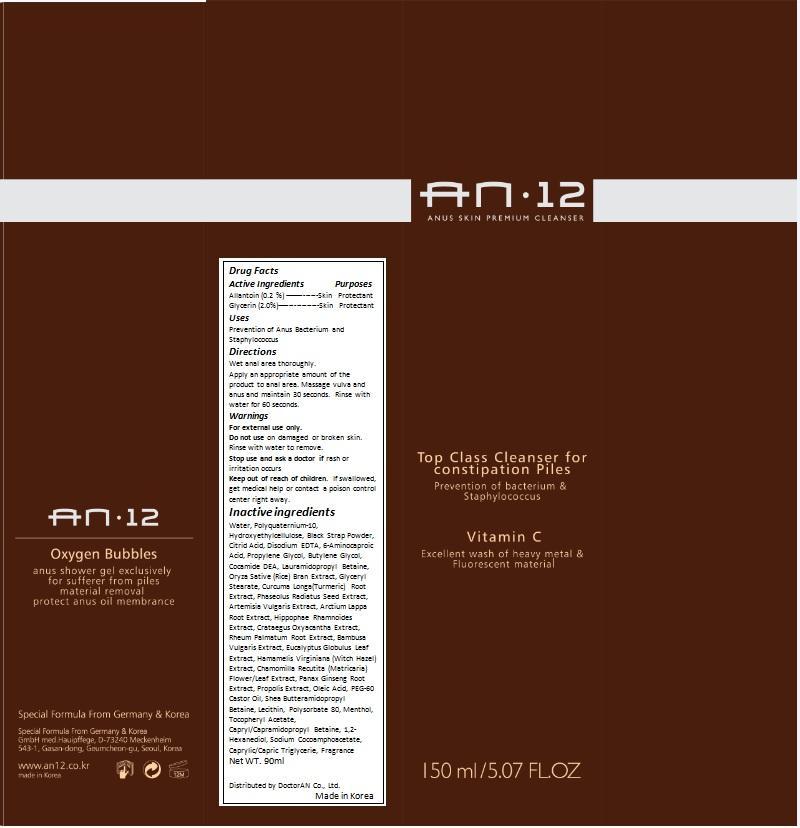 DRUG LABEL: AN12
NDC: 69318-001 | Form: GEL
Manufacturer: DoctorAN
Category: otc | Type: HUMAN OTC DRUG LABEL
Date: 20141024

ACTIVE INGREDIENTS: ALLANTOIN 0.3 mg/150 mL; GLYCERIN 3 mg/150 mL
INACTIVE INGREDIENTS: WATER; HYDROXYETHYL CELLULOSE (2000 MPA.S AT 1%); SPANISH SARDINE; CITRIC ACID MONOHYDRATE; EDETATE DISODIUM; BUTYLENE GLYCOL; COCO GLUCOSIDE; Decyl Glucoside; COCO DIETHANOLAMIDE; CARICA PAPAYA LEAF; HOUTTUYNIA CORDATA FLOWERING TOP; NEPIDERMIN; RICE BRAN; ARTEMISIA VULGARIS ROOT; MUNG BEAN; CENTELLA ASIATICA; PURSLANE; RHEUM PALMATUM ROOT; BAMBUSA VULGARIS TOP; EUCALYPTUS GLOBULUS LEAF; HAMAMELIS VIRGINIANA TOP; MATRICARIA RECUTITA FLOWERING TOP; PROPOLIS WAX; OLEIC ACID; PEG-60 CASTOR OIL; POMEGRANATE; ASCORBIC ACID; Polysorbate 80; MENTHOL; 1,2-HEXANEDIOL

Drug Facts

ACTIVE INGREDIENT

Dimethicone 1%

Allantoin 2%

PURPOSE

Skin Protectant

INDICATIONS AND USAGE

Breast Essence to help skin elasticity and beauty

WARNINGS

For external use only.

Do not use on damaged or broken skin.

Stop use and ask a doctor if rash or irritation, red spots, and swelling occur.

Keep out of reach of children.

When using this product, keep out of eyes.

INSTRUCTIONS FOR USE

Apply breast essence every morning and evening.

INACTIVE INGREDIENT

Pure water, Butylene glycol, Anemarrhena asphodeloides bunge extract, Propylene glycol, Cetyl alcohol, Glyceryl stearate/PEG-100-Stearate, Betaine, Arbutin, Phytrogen, Sorbitan sesquioleate, Polysorbate 80, Sorbitan stearate, Macadamia ternifolia seed oil, Simmondsia chinensis seed oil, Dipotassium glycyrrhizate, Triethanolamine, 1,2-hexandediol, Adenosine, Carbomer, Tocopheryl acetate, Sodium hyaluronate, Cultured wild ginseng roots extracts, Rose extract, Soybean extract, Portulaca oleracea extract, Perfume

DOSAGE AND ADMINISTRATION

Apply appropriate amount of essence every morning and evening.